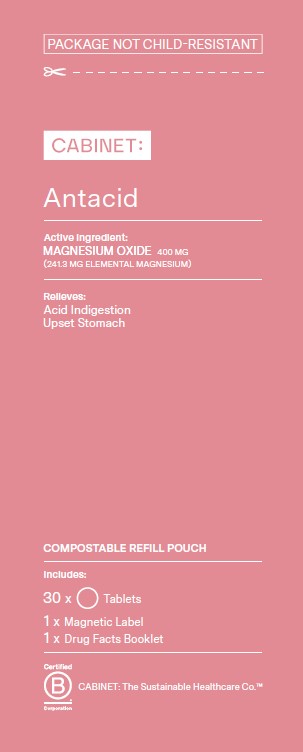 DRUG LABEL: Antacid
NDC: 68210-4171 | Form: TABLET
Manufacturer: Spirit Pharmaceuticals LLC
Category: otc | Type: HUMAN OTC DRUG LABEL
Date: 20241209

ACTIVE INGREDIENTS: MAGNESIUM OXIDE 400 mg/1 1
INACTIVE INGREDIENTS: CROSCARMELLOSE SODIUM; MICROCRYSTALLINE CELLULOSE; STEARIC ACID; SILICON DIOXIDE

Antacid

Active Ingredient (in each tablet)

Magnesium oxide 400 mg

(241.3 mg Elemental Magnesium)

Purpose

Antacid

Uses

relieves • acid indigestion • upset stomach

Ask a doctor before use if you have

kidney disease

Ask a doctor or pharmacist before use if you are

taking a prescription drug. Antacids may interact with certain prescription drugs.

Do not take

more than 2 tablets in a 24 hour period or use the maximum dosage of this product for more than two weeks, except under the advise and under supervision of a physician. May have a laxative effect.

If pregnant or breast-feeding,

ask a health professional before use.

Directions

• take 1 tablet twice a day or as directed by physician

Other information

• Magnesium content per tablet: 240 mg
• store at controlled room temperature 15° to 30°C (59° to 86°F)

Inactive ingredients

Colloidal silicon dioxide, croscarmellose sodium, microcrystalline cellulose, stearic acid

Questions or comments?

1-888-333-9792

Distributed by:

Cabinet Health P.B.C.

Principal Display

PACKAGE NOT CHILD-RESISTANT

CABINET

Antacid

Active ingredient:
MAGNESIUM OXIDE 400 MG
(241.3 MG ELEMENTAL MAGNESIUM)

Relieves:
Acid Indigestion
Upset Stomach

COMPOSTABLE REFILL POUCH

30 Tablets

1 x Magnetic Label

1 x Drug Facts Booklet

CABINET: The Sustainable Healthcare Co.™